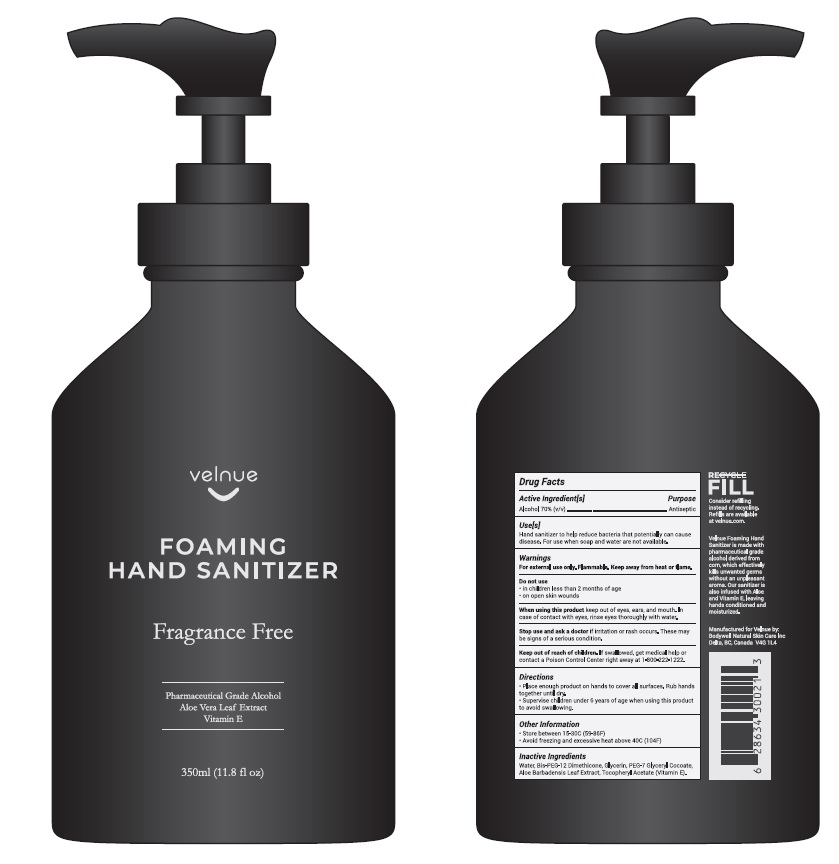 DRUG LABEL: Velnue
NDC: 81441-003 | Form: LIQUID
Manufacturer: Bodywell Natural Skin Care Inc
Category: otc | Type: HUMAN OTC DRUG LABEL
Date: 20210123

ACTIVE INGREDIENTS: ALCOHOL 70 mL/100 mL
INACTIVE INGREDIENTS: WATER; BIS-PEG-12 DIMETHICONE (70 MPA.S); PEG-7 GLYCERYL COCOATE; GLYCERIN; ALOE VERA LEAF; .ALPHA.-TOCOPHEROL ACETATE

Velnue FOAMING HAND SAITIZER Fragrance Free

Active Ingredients

Ethanol 70%

Purpose

Antiseptic.

Uses

- Hand Sanitizer to help reduce bacteria that potentially can cause disease.
- For use when soap and water are not available.

Warnings

For external use only Flammable. Keep away from heat or flame.

Do not use• in children less than 2 months of age.
• on open skin or wounds.

When using this product keep out of eyes, ears and mouth. In case of contact with eyes, rinse eyes thoroughly with water.

Stop use and ask a doctor

- if irritation occurs.
- These may be signs of a serious condition.

Keep out of reach of children.

If swallowed, get medical help or contact a Poison Control Center right away.

Directions.

• Place enough product on hands to cover all surfaces. Rub hands together until dry.
• Supervise children under 6 years of age when using this product to avoid swallowing.

Other Information.

• Store between 15-30C (59-86F)
• Avoid freezing & excessive heat above 40C(104F)

Inactive Ingredients.

Aqua, Bis-PEG-12 Dimethicone, Glycerin, PEG-7 Glyceryl Cocoate, Aloe Barbadensis Leaf Extract, Tocopheryl Acetate (Vitamin E).